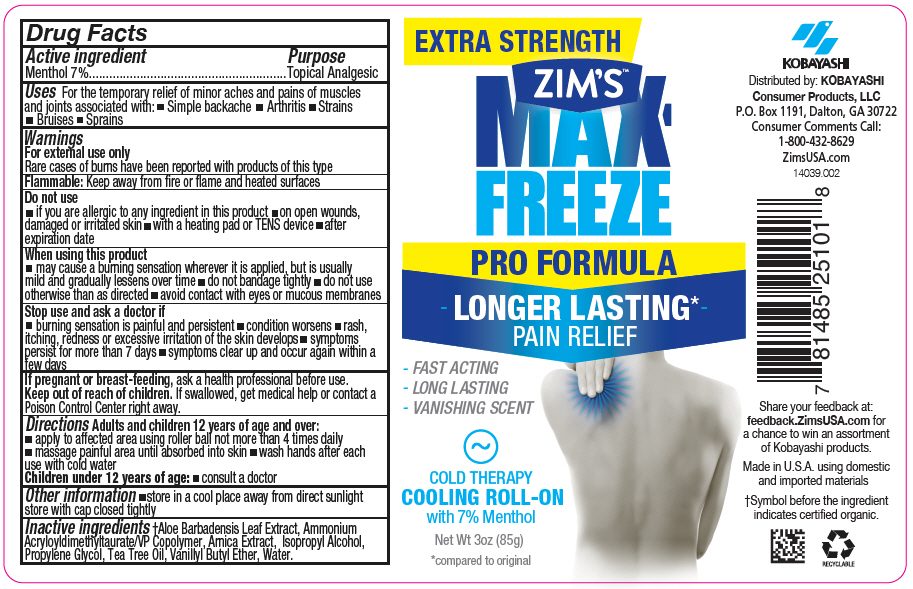 DRUG LABEL: ZIMS MAX FREEZE 
NDC: 54273-007 | Form: GEL
Manufacturer: KOBAYASHI Healthcare International, Inc.
Category: otc | Type: HUMAN OTC DRUG LABEL
Date: 20231116

ACTIVE INGREDIENTS: MENTHOL, UNSPECIFIED FORM 70 mg/1 g
INACTIVE INGREDIENTS: ALOE VERA LEAF; ARNICA MONTANA WHOLE; VANILLYL BUTYL ETHER; WATER; PROPYLENE GLYCOL; TEA TREE OIL; ISOPROPYL ALCOHOL; HYDROXYPROPYL CELLULOSE, UNSPECIFIED

ZIM'S™ MAX FREEZE
PRO FORMULA

Drug Facts

Active ingredient

Menthol 7%

Purpose

Topical Analgesic

Uses

For the temporary relief of minor aches and pains of muscles and joints associated with:

- Simple backache
- Arthritis
- Strains
- Bruises
- Sprains

Warnings

For external use only

Rare cases of burns have been reported with products of this type

Flammable: Keep away from fire or flame and heated surfaces

Do not use

- if you are allergic to any ingredient in this product
- on open wounds, damaged or irritated skin
- with a heating pad or TENS device
- after expiration date

When using this product

- may cause a burning sensation wherever it is applied, but is usually mild and gradually lessens over time
- do not bandage tightly
- do not use otherwise than as directed
- avoid contact with eyes or mucous membranes

Stop use and ask a doctor if

- burning sensation is painful and persistent
- condition worsens
- rash, itching, redness or excessive irritation of the skin develops
- symptoms persist for more than 7 days
- symptoms clear up and occur again within a few days

PREGNANCY OR BREAST FEEDING

If pregnant or breast-feeding, ask a health professional before use.

Keep out of reach of children. If swallowed, get medical help or contact a Poison Control Center right away.

Directions

Adults and children 12 years of age and over:

- apply to affected area using roller ball not more than 4 times daily
- massage painful area until absorbed into skin
- wash hands after each use with cold water

Children under 12 years of age:

- consult a doctor

Other information

- store in a cool place away from direct sunlight
  store with cap closed tightly

Inactive ingredients

[Symbol before the ingredient indicates certified organic.] Aloe Barbadensis Leaf Extract, Ammonium Acryloyldimethyltaurate/VP Copolymer, Arnica Extract, Isopropyl Alcohol, Propylene Glycol, Tea Tree Oil, Vanillyl Butyl Ether, Water.

QUESTIONS

Consumer Comments Call:
1-800-432-8629

Distributed by: KOBAYASHI
Consumer Products, LLC
P.O. Box 1191, Dalton, GA 30722

PRINCIPAL DISPLAY PANEL - 85 g Bottle Label

EXTRA STRENGTH

ZIM'S™
MAX-
FREEZE

PRO FORMULA

- LONGER LASTING* -
PAIN RELIEF

- FAST ACTING
- LONG LASTING
- VANISHING SCENT

COLD THERAPY
COOLING ROLL-ON
with 7% Menthol

Net Wt 3oz (85g)

*compared to original